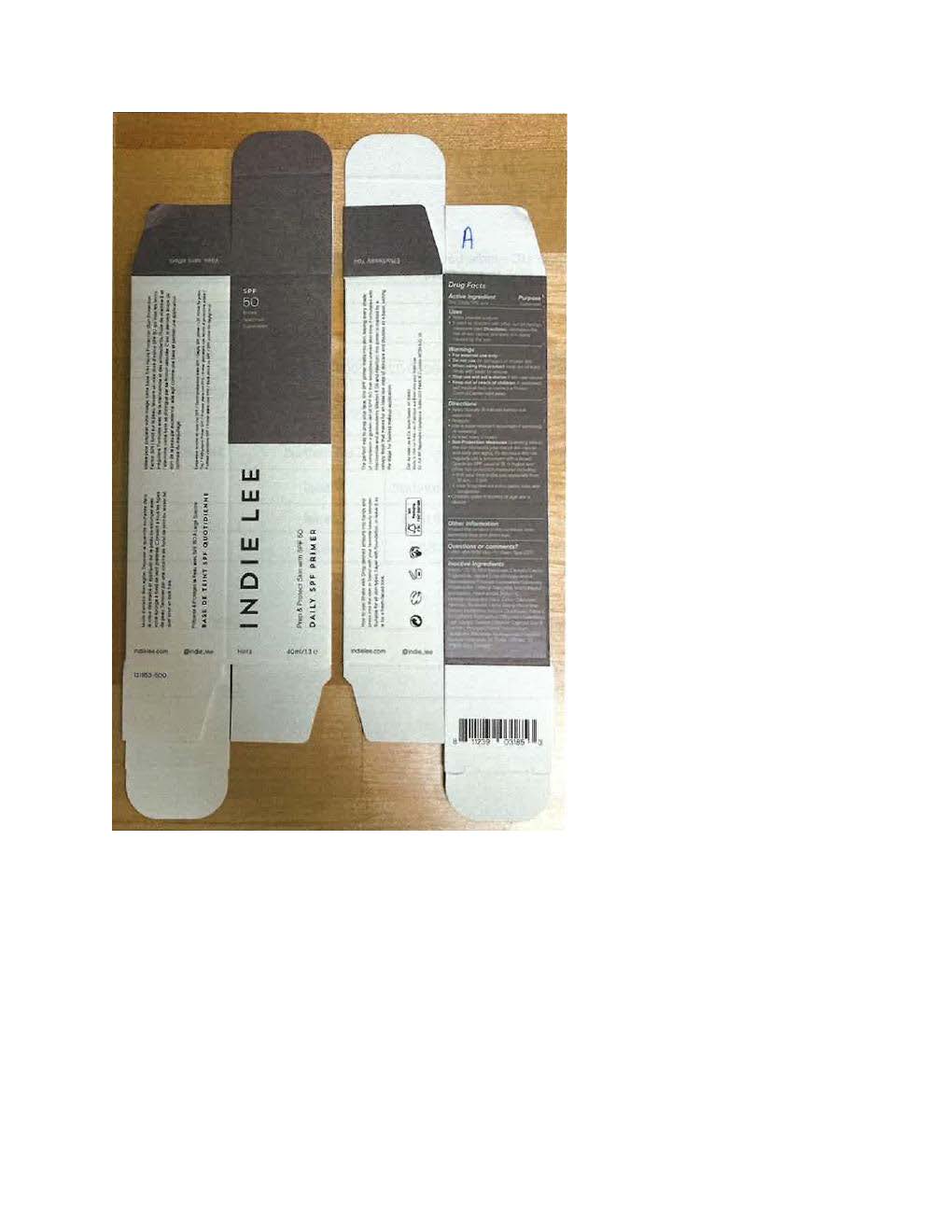 DRUG LABEL: Indie Lee Daily Primer
NDC: 78870-245 | Form: LOTION
Manufacturer: America Exchange
Category: otc | Type: HUMAN OTC DRUG LABEL
Date: 20251106

ACTIVE INGREDIENTS: ZINC OXIDE 132 mg/1 mL
INACTIVE INGREDIENTS: ROSMARINUS OFFICINALIS FLOWER; TETRASODIUM GLUTAMATE DIACETATE; SODIUM HYDROXIDE; SODIUM CHLORIDE; POLYGLYCERYL-4 DIISOSTEARATE/POLYHYDROXYSTEARATE/SEBACATE; CAPRYLIC/CAPRIC TRIGLYCERIDE; TRIDECYL SALICYLATE; ORYZA SATIVA WHOLE; WATER; NIACINAMIDE; NYLON-12; COCO-CAPRYLATE; HYDROLYZED JOJOBA ESTERS; .ALPHA.-BISABOLOL, (+)-; ALKYL (C12-15) BENZOATE; PROPANEDIOL; LECITHIN, SOYBEAN; ALLANTOIN; SILICON DIOXIDE; TOCOPHEROL; CAPRYLYL GLYCOL; PHENYLPROPANOL; HELIANTHUS ANNUUS FLOWERING TOP; METHYLPROPANEDIOL; POLYGLYCERYL-2 DIPOLYHYDROXYSTEARATE; POLYGLYCERYL-3 DIISOSTEARATE; STEARALKONIUM HECTORITE; FERRIC OXIDE RED; FERRIC OXIDE YELLOW; FERROSOFERRIC OXIDE

Indie Lee Daily Primer